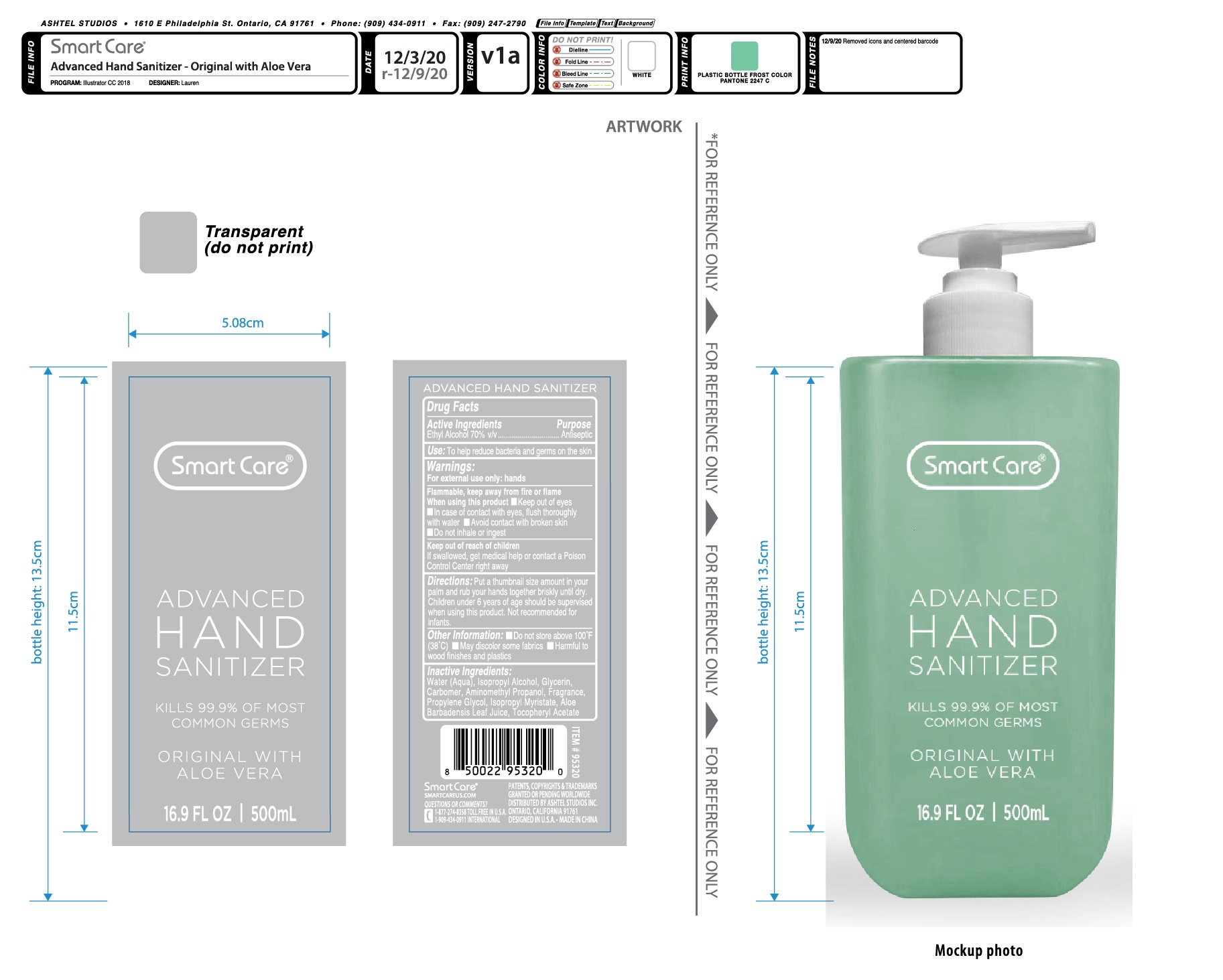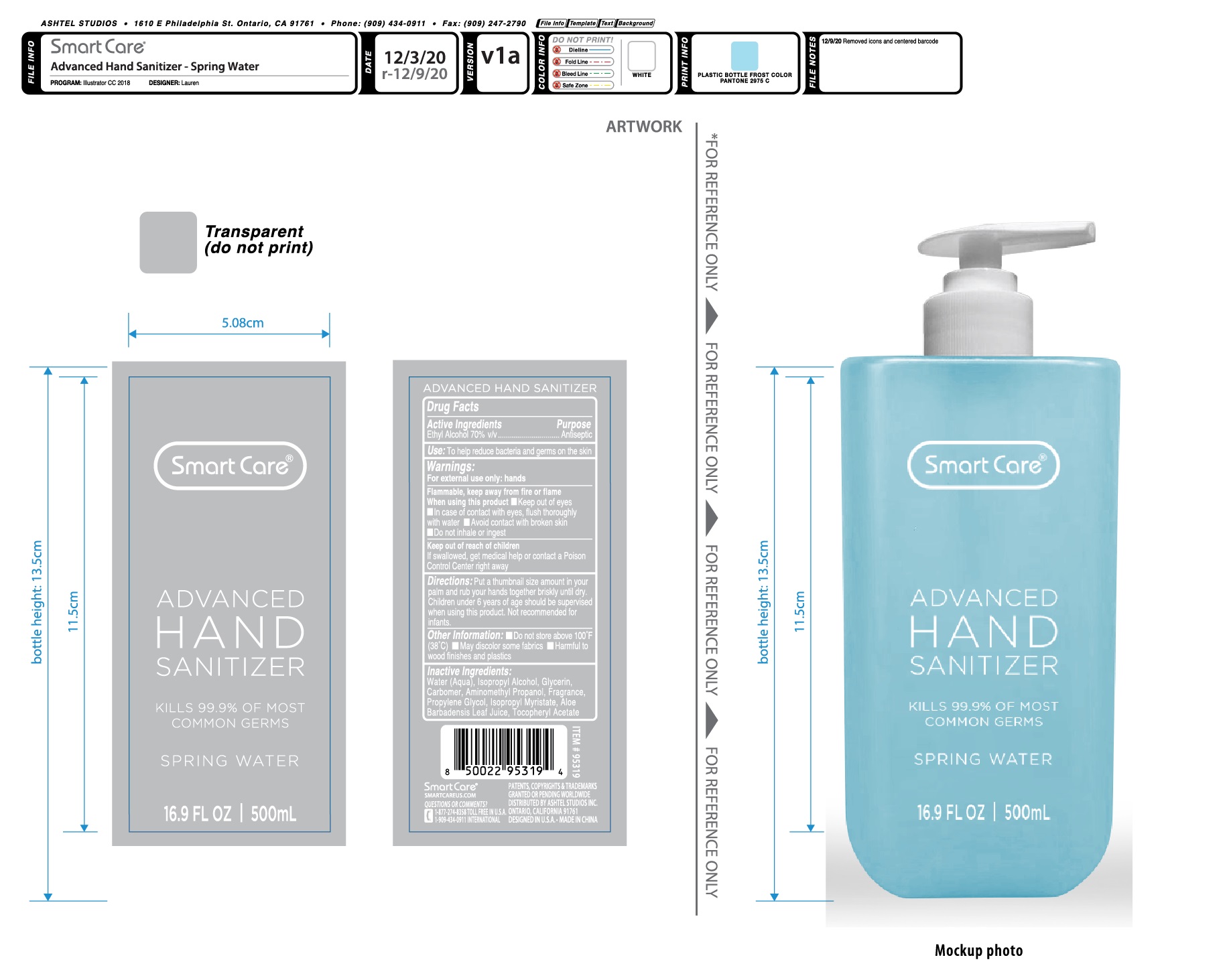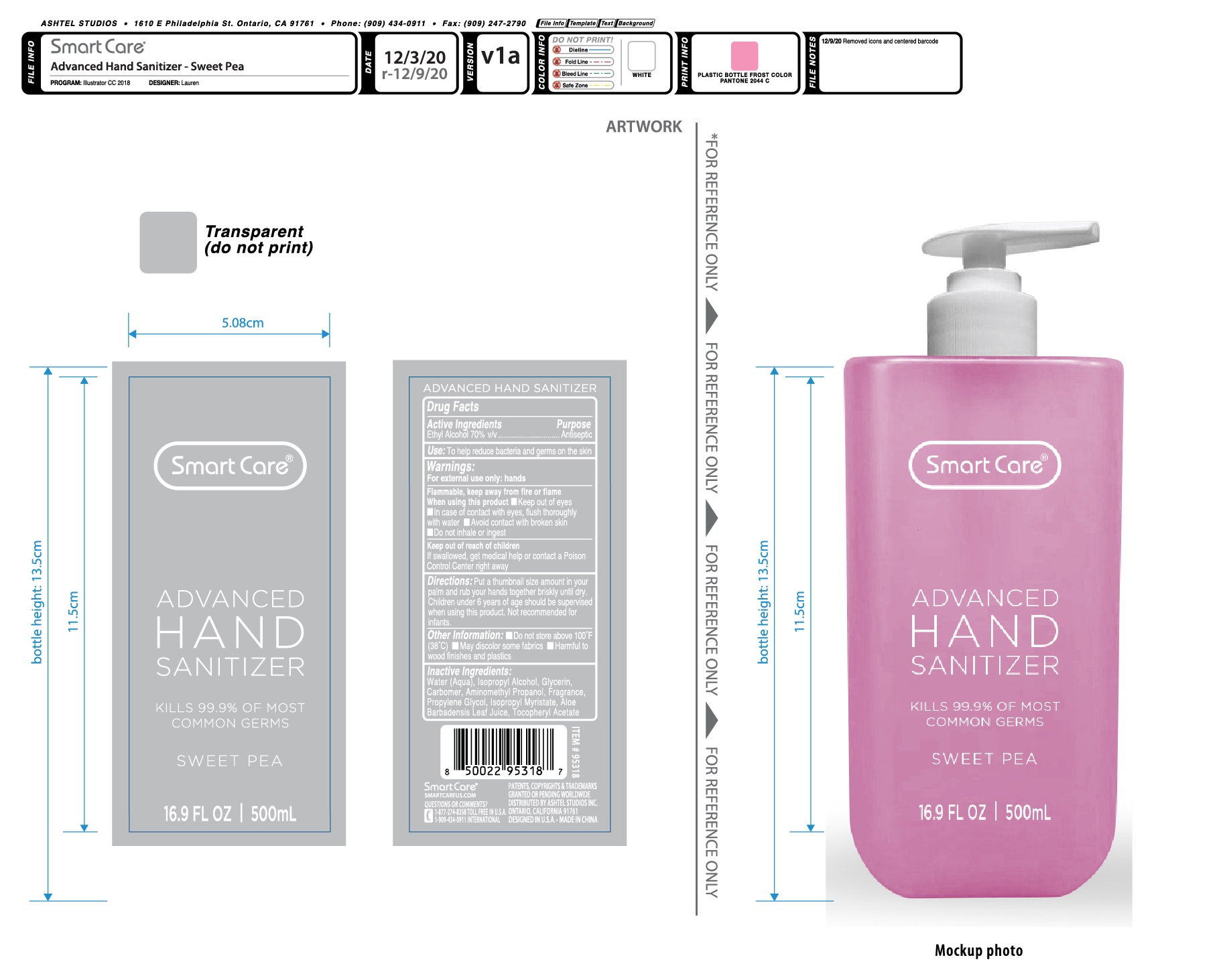 DRUG LABEL: Smart Care Advance Hand Sanitizer 16.9oz
NDC: 54860-407 | Form: GEL
Manufacturer: Shenzhen Lantern Scicence Co.,Ltd.
Category: otc | Type: HUMAN OTC DRUG LABEL
Date: 20230512

ACTIVE INGREDIENTS: ALCOHOL 70 mL/100 mL
INACTIVE INGREDIENTS: ISOPROPYL ALCOHOL 0.1 mL/100 mL; PROPYLENE GLYCOL 0.1 mL/100 mL; ALOE VERA LEAF 0.01 mL/100 mL; WATER 29.068 mL/100 mL; GLYCERIN 0.1 mL/100 mL; AMINOMETHYLPROPANOL 0.12 mL/100 mL; CARBOMER 940 0.3 mL/100 mL; VANILLA 0.2 mL/100 mL; ISOPROPYL MYRISTATE 0.001 mL/100 mL; .ALPHA.-TOCOPHEROL ACETATE 0.001 mL/100 mL

Smart Care Advance Hand Sanitizer 16.9oz

Drug Facts

Active Ingredient

Active Ingredient Purpose

Ethyl Alcohol 70%V/V Antiseptic

Use

Health care personel hand rub to help reduce bacteria that potentially can cause disease.

use

To help reduce bacteria and germs on the skin.

Warning

For external use only;hands

Flammable,keep away from fire or flame.

WARNINGS AND PRECAUTIONS

For external use only.

Flammable, keep away from heat and flame.

STOP USE

Discontinue if skin becomes irritated and ask a doctor .

Keep out of reach of children. In case of accidental ingestion, seek professional assistance or contact a poson control center immediately.

keep out of reach of children

If swallowed,get medical help or contact a Poison Control Center right away.

DOSAGE AND ADMINISTRATION

Recommended for repeated use.

use anywhere without water.

Directions

Put a thumbnail size amount in your palm and rub your hands together briskly until dry.Children under 6 years of age should be supervised when using this product.Not recommended for infants.

When using this product

keep out of eyes. In case of contact with eyes, flush thoroughly with water.

Do not inhale or ingest.

Avoid contact with broken skin.

Other information

Do not store above 105F.

May discolor some fabrics.

Harmful to wood finishes and plastics.

Inactive ingredients

Alcohol，Aqua，Isopropyl Alcohol，Glycerin，Carbomer，Aminomethyl Propanol，Parfum，Propylene Glycol，Isopropyl Myristate，Aloe Barbadensis Leaf Water，Tocopheryl Acetate.

When using this product

Keep out of eyes,ears,and mouth.In case of contact with eyes,flush thoroughly with water.

avoid contact with broken skin.

do not inhale or ingest.

Other information

Do not store above 100℉（38℃）

May discolor some fabrics

Harmful to wood finishes and plastics.

PACKAGE LABEL

Packaging